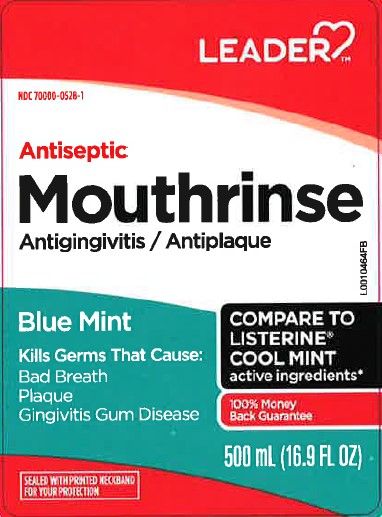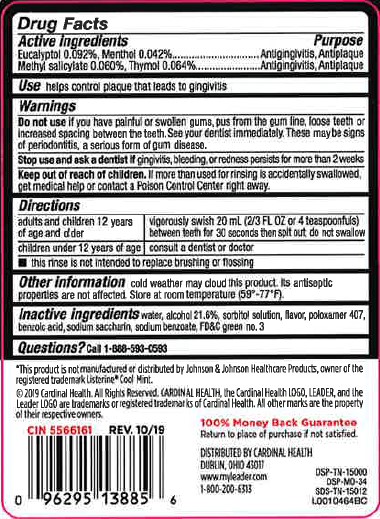 DRUG LABEL: Antiseptic
NDC: 70000-0528 | Form: MOUTHWASH
Manufacturer: Cardinal Health, 110 dba Leader
Category: otc | Type: HUMAN OTC DRUG LABEL
Date: 20260129

ACTIVE INGREDIENTS: EUCALYPTOL 0.92 mg/1 mL; MENTHOL 0.42 mg/1 mL; METHYL SALICYLATE 0.6 mg/1 mL; THYMOL 0.64 mg/1 mL
INACTIVE INGREDIENTS: WATER; ALCOHOL; SORBITOL; POLOXAMER 407; BENZOIC ACID; SACCHARIN SODIUM; SODIUM BENZOATE; FD&C GREEN NO. 3

Leader 664.003/664AU
Blue Mint Antiseptic Mouthrinse

Active ingredient

Eucalyptol 0.092%

Menthol 0.042%

Methyl salicylate 0.060%

Thymol 0.064%

Purpose

Antigingivitis, Antiplaque

Use

helps control plaque that leads to gingivitis

Warnings

for this product

Do not use

if you have painful or swollen gums, pus from the gum line, loose teeth or increased spacing between the teeth. See your dentist immediately. These may be signs of periodontitis, a serious form of gum disease.

Stop use and ask a dentist if

gingivitis, bleeding, or redness persists for more than 2 weeks

Keep out of reach of children.

If more than used for rinsing is accidentally swallowed, get medical help or contact a Poison Control Center right away.

Directions

adults and children 12 years of age and older - vigorously swish 20 mL (2/3 FL OZ or 4 teaspoonfuls) between teeth for 30 seconds then spit out; do not swallow

children under 12 years of age - consult a dentist or doctor

- this rinse is not intended to replace brushing or flossing

other information

cold weather may cloud this product. Its antiseptic properties are not affected. Store at room temperature (59°-77°F).

inactive ingredients

water, alcohol 21.6%, sorbitol solution, flavor, poloxamer 407, benzoic acid, sodium saccharin, sodium benzoate, FD&C green no. 3

disclaimer

*This product is not manufactured or distributed by Johnson & Johnson Healthcare Products, owner of the registered trademark ListerineCool Mint.

ADVERSE REACTION

©2019 Cardinal Health. All Rights Reserved. CARDINAL HEALTH, the Cardinal Health LOGO, LEADER, and the Leader LOGO are trademarks or registered trademarks of Cardinal Health. All other marks are the property of their respective owners.

CIN 5566161 REV. 10/19

100% Money Back Guarantee

Return to place of purchase if not satisfied.

DISTRBUTED BY CARDINAL HEALTH

DUBLIN, OHIO, 43017

www.myleader.com

1-800-200-6313

DSP-TN-15000

DSP-MO-34

SDS-TN-15012

principal display panel

LEADER™

NDC 70000-0528-1

Antiseptic

Mothrinse

Antigingivitis/Antiplaque

Blue Mint

Kills Germs That Cause:

Bad Breath

Plaque

Gingivitis Gum Disease

COMPARE TO LISTERINE®COOL MINT active ingredients*

100% Money Back Guarantee

500 mL (16.9 FL OZ)

SEALED WITH PRINTED NECKBAND FOR YOUR PROTECTION